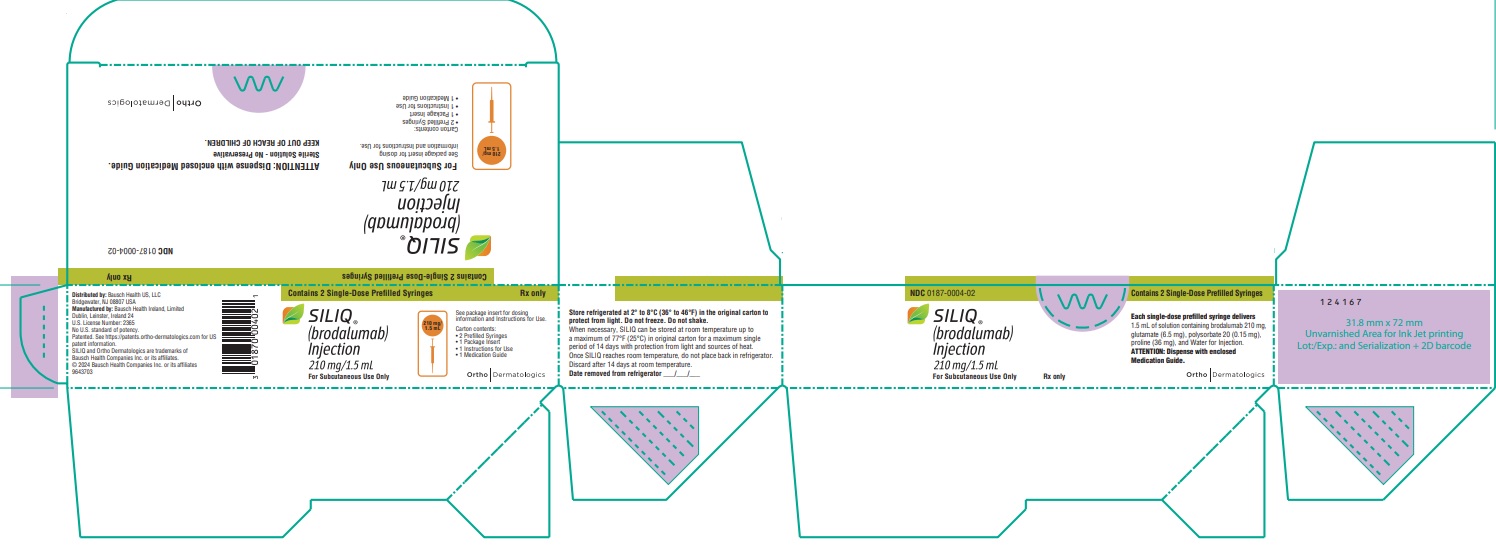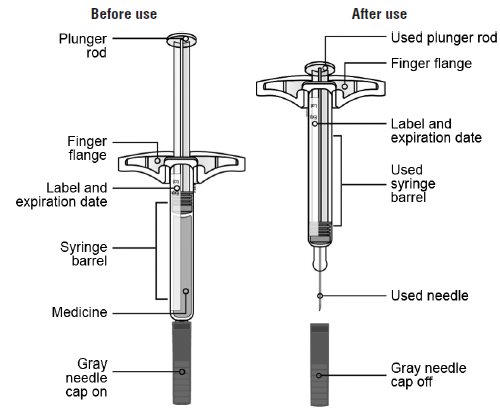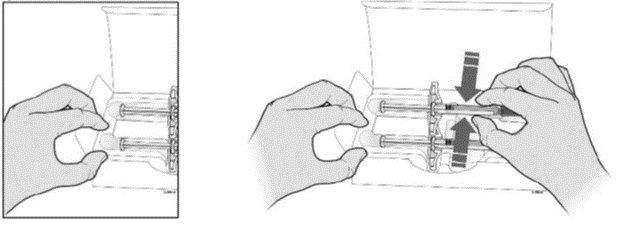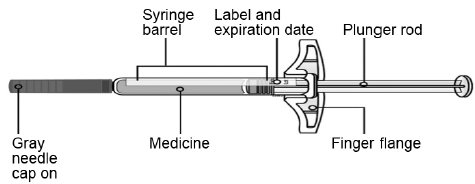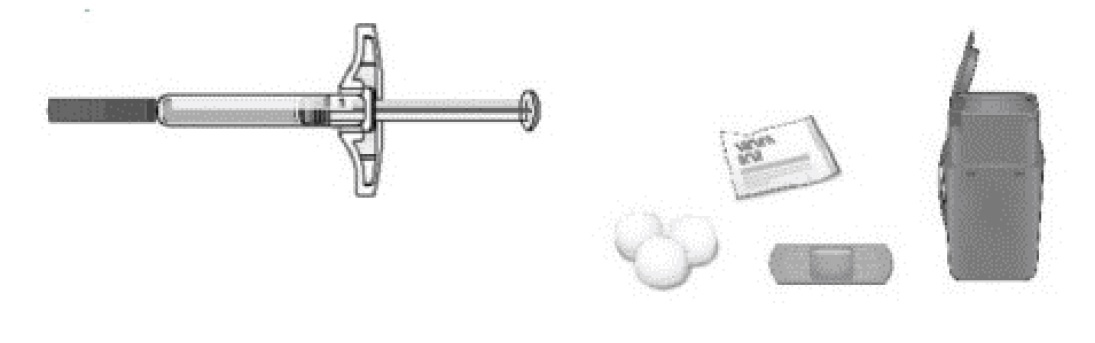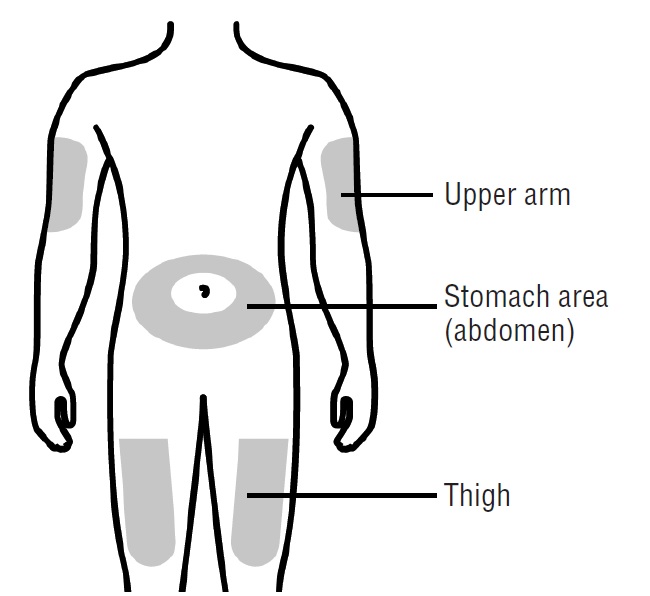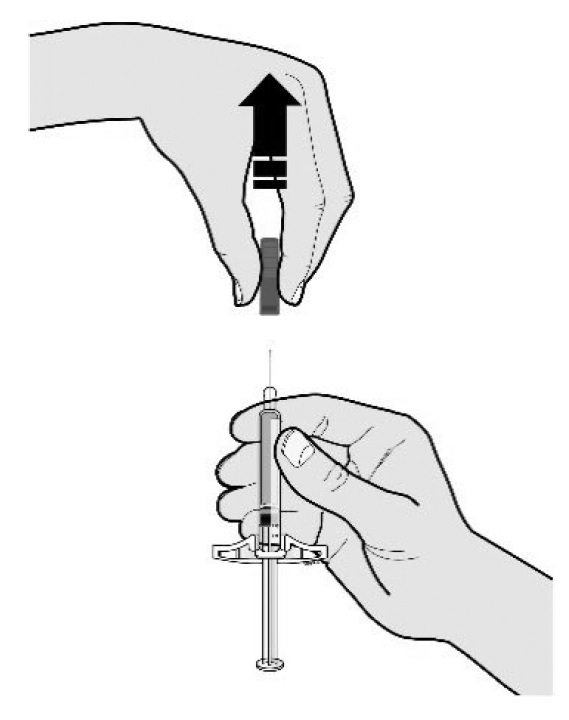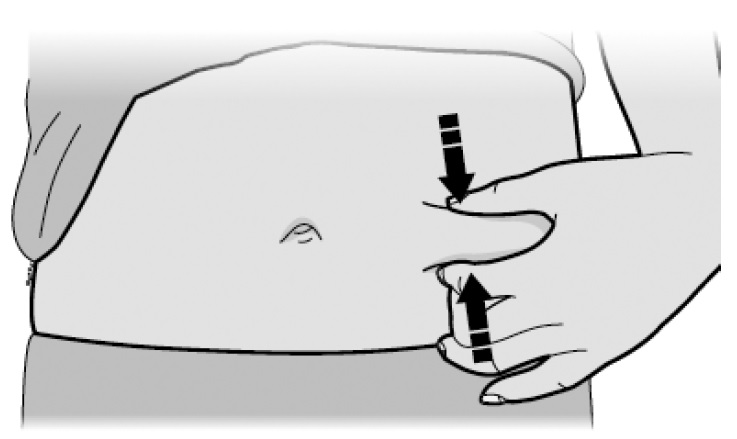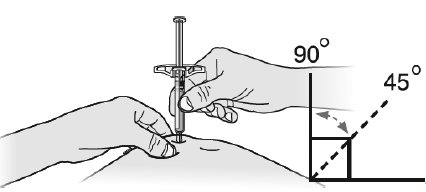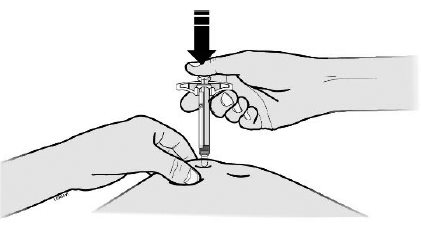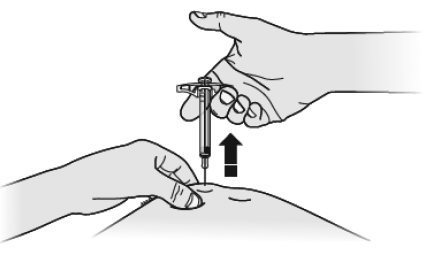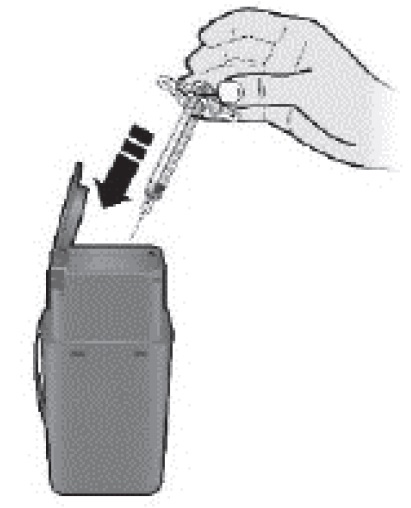 DRUG LABEL: Siliq
NDC: 0187-0004 | Form: INJECTION
Manufacturer: Bausch Health US LLC
Category: prescription | Type: HUMAN PRESCRIPTION DRUG LABEL
Date: 20260211

ACTIVE INGREDIENTS: BRODALUMAB 210 mg/1 1

HIGHLIGHTS OF PRESCRIBING INFORMATION

These highlights do not include all the information needed to use SILIQ safely and effectively. See full prescribing information for SILIQ.
SILIQ®(brodalumab) injection, for subcutaneous use
Initial U.S. Approval: 2017

WARNING: SUICIDAL IDEATION AND BEHAVIOR

See full prescribing information for complete boxed warning.

- Suicidal ideation and behavior, including completed suicides, have occurred in patients treated with SILIQ. (5.1, 6.1)
- Prior to prescribing, weigh potential risks and benefits in patients with a history of depression and/or suicidal ideation or behavior. (5.1)
- Patients with new or worsening suicidal thoughts and behavior should be referred to a mental health professional, as appropriate. (5.1)
- Advise patients and caregivers to seek medical attention for manifestations of suicidal ideation or behavior, new onset or worsening depression, anxiety, or other mood changes. (5.1)
- SILIQ is available only through a restricted program called the SILIQ REMS Program. (5.2)

RECENT MAJOR CHANGES

Contraindications (4) 08/2024

Warnings and Precautions, Hypersensitivity Reactions (5.3) 08/2024

1 INDICATIONS AND USAGE

SILIQ is a human interleukin-17 receptor A (IL-17RA) antagonist indicated for the treatment of moderate to severe plaque psoriasis in adult patients who are candidates for systemic therapy or phototherapy and have failed to respond or have lost response to other systemic therapies. (1)

2 DOSAGE AND ADMINISTRATION

Administer 210 mg of SILIQ by subcutaneous injection at Weeks 0, 1, and 2 followed by 210 mg every 2 weeks. (2.2)

3 DOSAGE FORMS AND STRENGTHS

Injection: 210 mg/1.5 mL solution in a single-dose prefilled syringe. (3)

4 CONTRAINDICATIONS

- Crohn’s disease (4)
- Clinically significant hypersensitivity to brodalumab or to any of the excipients in SILIQ or component of the container (4)

5 WARNINGS AND PRECAUTIONS

- Hypersensitivity Reactions:Serious hypersensitivity reactions, including anaphylaxis, may occur. If a serious hypersensitivity reaction occurs, immediately discontinue SILIQ and initiate appropriate therapy. (5.3)
- Infections:Serious infections have occurred. Consider the risks and benefits prior to initiating SILIQ in patients with a chronic infection or a history of recurrent infection. Instruct patients to seek medical advice if signs or symptoms of clinically important chronic or acute infection occur. If a serious infection develops, discontinue SILIQ until the infection resolves. (5.4)
- Tuberculosis (TB):Evaluate patients for TB infection prior to initiating treatment with SILIQ. (5.5)
- Eczematous Eruptions:The onset of eczematous eruptions was variable, ranging from days to months after the first dose of SILIQ. Some cases of severe eczematous eruptions resulted in hospitalization. Treatment may need to be discontinued to resolve the eczematous eruption. Some patients with limited psoriasis treatment options were successfully treated for eczema while continuing SILIQ. (5.6)
- Crohn’s Disease:Crohn’s disease occurred during clinical trials. Discontinue SILIQ if patient develops Crohn’s disease while taking SILIQ. (5.7)
- Immunizations:Avoid using live vaccines concurrently with SILIQ. (5.8)

6 ADVERSE REACTIONS

Most common adverse reactions (incidence ≥1%) were arthralgia, headache, fatigue, diarrhea, oropharyngeal pain, nausea, myalgia, injection site reactions, influenza, neutropenia, and tinea infections. (6.1)

To report SUSPECTED ADVERSE REACTIONS, contact Bausch Health US, LLC at 1-800-321-4576 or FDA at 1-800-FDA-1088 or www.fda.gov/medwatch.

FULL PRESCRIBING INFORMATION

WARNING: SUICIDAL IDEATION AND BEHAVIOR

Suicidal ideation and behavior, including completed suicides, have occurred in patients treated with SILIQ. Prior to prescribing SILIQ, weigh the potential risks and benefits in patients with a history of depression and/or suicidal ideation or behavior. Patients with new or worsening suicidal ideation and behavior should be referred to a mental health professional, as appropriate. Advise patients and caregivers to seek medical attention for manifestations of suicidal ideation or behavior, new onset or worsening depression, anxiety, or other mood changes [ see Warnings and Precautions(5.1) ].

Because of the observed suicidal behavior in subjects treated with SILIQ, SILIQ is available only through a restricted program under a Risk Evaluation and Mitigation Strategy (REMS) called the SILIQ REMS Program [see Warnings and Precautions(5.2) ].

1 INDICATIONS AND USAGE

SILIQ®(brodalumab) is indicated for the treatment of moderate to severe plaque psoriasis in adult patients who are candidates for systemic therapy or phototherapy and have failed to respond or have lost response to other systemic therapies.

2 DOSAGE AND ADMINISTRATION

2.1 Tuberculosis Assessment Prior to Initiation of SILIQ

Evaluate patients for tuberculosis (TB) infection prior to initiating treatment with SILIQ [see Warnings and Precautions (5.4)].

2.2 Dosage

The recommended SILIQ dose is 210 mg administered by subcutaneous injection at Weeks 0, 1, and 2 followed by 210 mg every 2 weeks.

If an adequate response has not been achieved after 12 to 16 weeks of treatment with SILIQ, consider discontinuing therapy. Continued treatment beyond 16 weeks in patients who have not achieved an adequate response is not likely to result in greater success.

2.3 Important Administration Instructions

Administer SILIQ subcutaneously. Each prefilled syringe is for single dose only.

Instruct patients to review the Medication Guide before use [see Medication Guide].SILIQ is intended for use under the guidance and supervision of a healthcare professional. Patients may self-inject SILIQ when deemed appropriate by a healthcare professional and after proper training in subcutaneous injection technique using the prefilled syringe.

Advise patients who are self-administering to inject the full dose and to read the Instructions for Use before administration [ see Instructions for Use].

Do not inject SILIQ into areas where the skin is tender, bruised, red, hard, thick, scaly, or affected by psoriasis.

2.4 Preparation of SILIQ Prefilled Syringe

- Allow SILIQ prefilled syringe to reach room temperature (approximately 30 minutes) before injecting. Do not warm in any other way. Do not remove the gray needle cap on the prefilled syringe while allowing it to reach room temperature.
- Visually inspect SILIQ for particles and discoloration prior to administration. SILIQ is a clear to slightly opalescent, colorless to slightly yellow solution. Do not use SILIQ if it is cloudy or discolored or if foreign matter is present.
- Instruct patients to use the prefilled syringe and to inject the full amount (1.5 mL), which provides 210 mg of SILIQ, according to the directions provided in the Instructions for Use [see Instructions for Use].

3 DOSAGE FORMS AND STRENGTHS

Injection: 210 mg/1.5 mL solution in a single-dose prefilled syringe. SILIQ is a clear to slightly opalescent, colorless to slightly yellow solution.

4 CONTRAINDICATIONS

SILIQ is contraindicated in patients with:

- Crohn’s disease because SILIQ may cause worsening of disease [see Warnings and Precautions (5.7)].
- Clinically significant hypersensitivity to brodalumab or to any of the excipients in SILIQ or component of the container. Hypersensitivity reactions, including anaphylaxis, have been reported with postmarket use of SILIQ [see Warnings and Precautions (5.3)].

5 WARNINGS AND PRECAUTIONS

5.1 Suicidal Ideation and Behavior

Suicidal ideation and behavior, including four completed suicides, occurred in subjects treated with SILIQ in the psoriasis clinical trials. There were no completed suicides in the 12-week placebo-controlled portion of the trials. SILIQ users with a history of suicidality or depression had an increased incidence of suicidal ideation and behavior as compared to users without such a history [see Adverse Reactions (6.1)].A causal association between treatment with SILIQ and increased risk of suicidal ideation and behavior has not been established.

Prescribers should weigh the potential risks and benefits before using SILIQ in patients with a history of depression or suicidality. Patients with new or worsening symptoms of depression or suicidality should be referred to a mental health professional, as appropriate. Advise patients and caregivers to seek medical attention for manifestations of suicidal ideation and behavior, new onset or worsening depression, anxiety, or other mood changes. Prescribers should also re-evaluate the risks and benefits of continuing treatment with SILIQ if such events occur.

Because of the observed suicidal ideation and behavior in subjects treated with SILIQ, if an adequate response to SILIQ has not been achieved within 12 to 16 weeks, consider discontinuing therapy.

SILIQ is available only through a restricted program under a REMS [ see Warnings and Precautions (5.2)].

5.2 SILIQ REMS Program

SILIQ is available only through a restricted program under a REMS called the SILIQ REMS Program because of the observed suicidal ideation and behavior in subjects treated with SILIQ [ see Warnings and Precautions (5.1)].

Notable requirements of the SILIQ REMS Program include the following:

- Prescribers must be certified with the program.
- Patients must sign a Patient-Prescriber Agreement Form.
- Pharmacies must be certified with the program and must only dispense to patients who are authorized to receive SILIQ.

Further information, including a list of qualified pharmacies, is available at www.SILIQREMS.com or by calling the SILIQ REMS Program Call Center at 855-511-6135.

5.3 Hypersensitivity Reactions

Serious hypersensitivity reactions, including anaphylaxis, have been reported with postmarket use of SILIQ. Some cases required hospitalization. If a serious hypersensitivity reaction occurs, immediately discontinue SILIQ and initiate appropriate therapy.

5.4 Infections

SILIQ may increase the risk of infections. In clinical trials, subjects treated with SILIQ had a higher rate of serious infections than subjects treated with placebo (0.5% versus 0.2%) and higher rates of fungal infections (2.4% versus 0.9%). One case of cryptococcal meningitis occurred in a subject treated with SILIQ during the 12-week randomized treatment period and led to discontinuation of therapy [see Adverse Reactions (6.1)].

During the course of clinical trials for plaque psoriasis, the exposure-adjusted rates for infections and serious infections were similar in the subjects treated with SILIQ and those treated with ustekinumab.

In patients with a chronic infection or a history of recurrent infection, consider the risks and benefits prior to prescribing SILIQ. Instruct patients to seek medical help if signs or symptoms of clinically important chronic or acute infection occur. If a patient develops a serious infection or is not responding to standard therapy for the infection, monitor the patient closely and discontinue SILIQ therapy until the infection resolves.

5.5 Risk for Latent Tuberculosis Reactivation

Evaluate patients for tuberculosis (TB) infection prior to initiating treatment with SILIQ. Do not administer SILIQ to patients with active TB infection. Initiate treatment for latent TB prior to administering SILIQ.

Consider anti-TB therapy prior to initiation of SILIQ in patients with a past history of latent or active TB in whom an adequate course of treatment cannot be confirmed. Closely monitor patients receiving SILIQ for signs and symptoms of active TB during and after treatment.

5.6 Eczematous Eruptions

Postmarketing cases of severe eczematous eruptions, including atopic dermatitis-like eruptions, were reported in patients receiving SILIQ. The onset of eczematous eruptions was variable, ranging from days to months after the first dose of SILIQ. Some cases of severe eczematous eruptions resulted in hospitalization. Treatment may need to be discontinued to resolve the eczematous eruption. Some patients with limited psoriasis treatment options were successfully treated for eczema while continuing SILIQ.

5.7 Crohn’s Disease

In psoriasis trials, which excluded subjects with active Crohn’s disease, Crohn’s disease occurred in one subject during treatment with SILIQ and led to discontinuation of therapy. In other trials, exacerbation of Crohn’s disease was observed with SILIQ use.

SILIQ is contraindicated in patients with Crohn’s disease.

Discontinue SILIQ if the patient develops Crohn’s disease while taking SILIQ.

5.8 Immunizations

Avoid use of live vaccines in patients treated with SILIQ. No data are available on the ability of live or inactive vaccines to elicit an immune response in patients being treated with SILIQ.

6 ADVERSE REACTIONS

The following serious adverse reactions are discussed in greater detail in other sections of labeling:

- Suicidal Ideation and Behavior [see Warnings and Precautions (5.1)]
- Hypersensitivity Reactions [see Warnings and Precautions (5.3)]
- Infections [ see Warnings and Precautions (5.4)]
- Crohn’s Disease [see Contraindications (4), Warnings and Precautions (5.7)]

6.1 Clinical Trial Experience

Because clinical trials are conducted under widely varying conditions, adverse reaction rates observed in the clinical trials of a drug cannot be directly compared to rates in the clinical trials of another drug and may not reflect the rates observed in practice.

The overall safety population included 4,558 subjects (3,066 SILIQ, 613 ustekinumab, 879 placebo) in controlled clinical trials and open-label extension studies. The majority of subjects were male (69%), white (91%), and aged 40-64 years old (58%). One third of subjects reported previous biologic use prior to enrollment. Across the clinical development program, 4,464 subjects received at least one dose of SILIQ; 3,755 subjects were exposed to SILIQ for at least 1 year.

Weeks 0 to 12:

Data from one multicenter, randomized, placebo-controlled trial (Trial 1), two multicenter, randomized, placebo- and active-controlled trials (Trials 2 and 3), and one dose-finding trial (Trial 4) in plaque psoriasis were pooled to evaluate the safety of SILIQ (210 mg weekly at Weeks 0, 1, and 2, followed by treatments every 2 weeks [Q2W]) compared to placebo for up to 12 weeks after treatment initiation.

During the 12-week, randomized treatment period, about 1% of the subjects in the treatment groups (SILIQ, ustekinumab, and placebo) discontinued treatment because of adverse events. Adverse events leading to discontinuation of SILIQ included neutropenia, arthralgia, and urticaria. The proportion of subjects who developed serious adverse events was similar among the SILIQ, ustekinumab, and placebo groups.

Table 1summarizes the adverse reactions that occurred at a rate of at least 1% and at a higher rate in the SILIQ 210 mg Q2W group than in the placebo group during the 12-week randomized treatment period of the pooled trials.

Table 1: Adverse Reactions Occurring in ≥ 1% of Subjects in the SILIQ Group and More Frequently than in the Placebo Group in Plaque Psoriasis Trials through Week 12
Adverse Reactions | Placebo; (N=879); n (%) | SILIQ 210 mg every 2 weeks [Subjects receiving 210 mg of SILIQ at Weeks 0, 1, and 2, followed by treatment every 2 weeks during the 12-week period] (N=1,496) n (%) | Ustekinumab (N=613) [Trials 2 and 3 included the active comparator, ustekinumab] n (%)
Arthralgia | 29 (3.3) | 71 (4.7) | 15 (2.4)
Headache | 31 (3.5) | 64 (4.3) | 23 (3.8)
Fatigue | 10 (1.1) | 39 (2.6) | 16 (2.6)
Diarrhea | 10 (1.1) | 33 (2.2) | 5 (0.8)
Oropharyngeal pain | 10 (1.1) | 31 (2.1) | 8 (1.3)
Nausea | 10 (1.1) | 28 (1.9) | 6 (1.0)
Myalgia | 3 (0.3) | 26 (1.7) | 4 (0.7)
Injection site reactions; (pain, erythema, bruising, hemorrhage, pruritus) | 11 (1.3) | 23 (1.5) | 12 (2.0)
Influenza | 4 (0.5) | 19 (1.3) | 7 (1.1)
Neutropenia | 4 (0.5) | 15 (1.0) | 5 (0.8)
Tinea infections; (tinea pedis, versicolor, cruris) | 2 (0.2) | 15 (1.0) | 3 (0.5)

Adverse reactions that occurred in less than 1% of subjects in the SILIQ group through Week 12 were conjunctivitis and candida infections (including oral [0.2%], genital [0.1%], and esophageal [0.1%] versus none in the placebo group).

Week 0 to End of Trial:

Through Week 52, exposure-adjusted rates of serious adverse events were similar between subjects treated with SILIQ and those treated with ustekinumab. Through the end of the trial, the exposure-adjusted rates of treatment-emergent serious adverse events were similar to those seen in the 52-week period in the subjects treated with SILIQ.

Specific Adverse Reactions:

Suicidal Ideation and Behavior

During the 12-week randomized treatment period in the pooled trials, one subject in the SILIQ group attempted suicide and none in the placebo or ustekinumab groups. From initiation through Week 52 of the trials, suicidal ideation or behavior occurred in 7 of 4,019 subjects (0.2 per 100 subject-years) treated with SILIQ and in 2 of 613 subjects (0.4 per 100 subject-years) treated with ustekinumab.

During the course of the clinical trials for plaque psoriasis, suicidal ideation or behavior occurred in 34 of 4,464 subjects treated with SILIQ (0.37 per 100 subject-years). Eight of the 10 subjects who attempted or completed suicide had a history of depression and/or suicidal ideation or behavior [see Warnings and Precautions (5.1,5.2)].

Infections

During the 12-week randomized treatment period, infections occurred in 25.4% of the SILIQ group compared to 23.4% of the placebo group. The majority of infections consisted of nasopharyngitis, upper respiratory tract infection, pharyngitis, urinary tract infections, bronchitis, and influenza, and did not necessitate treatment discontinuation. The SILIQ group had a higher rate of fungal infections compared to the placebo group (1.8% vs 0.9%). The fungal infections were primarily non-serious skin and mucosal candida infections [ see Warnings and Precautions (5.4)].

Neutropenia

During the 12-week randomized treatment period, neutropenia occurred in 0.7% of subjects in the SILIQ group. Most adverse reactions of neutropenia were transient. In subjects with normal absolute neutrophil count (ANC) at baseline, a reduction in ANC occurred in 6.8% of subjects in the SILIQ group, compared to 3.3% in the ustekinumab group, and 3.6% in the placebo group. Neutropenia ≥ Grade 3 (< 1,000/mm^3) occurred in 0.5% of subjects in the SILIQ group compared to 0.2% of subjects in the ustekinumab group and none in the placebo group. From Week 0 to end of trial, the exposure-adjusted rate of treatment-emergent neutropenia was 0.4 per 100 subject-years (0.1 per 100 subject-years were ≥ Grade 3). No serious infections were associated with cases of neutropenia.

6.2 Immunogenicity

As with all therapeutic proteins, there is potential for immunogenicity with SILIQ. Approximately 3% of subjects treated with SILIQ developed antibodies to brodalumab through the 52-week treatment period. Of the subjects who developed antibodies to brodalumab, none had antibodies that were classified as neutralizing. However, the assay to test for neutralizing antibodies had limitations detecting neutralizing antibodies in the presence of brodalumab; therefore, the incidence of neutralizing antibody development could be underestimated.

The detection of antibody formation is highly dependent on the sensitivity and specificity of the assay. Additionally, the observed incidence of antibody (including neutralizing antibody) positivity in an assay may be influenced by several factors, including assay methodology, sample handling, timing of sample collection, concomitant medications, and underlying disease. For these reasons, comparison of the incidence of antibodies to SILIQ with the incidence of antibodies to other products may be misleading.

6.3 Postmarketing Experience

The following adverse reactions have been identified during post-approval use of SILIQ. Because these reactions are reported voluntarily from a population of uncertain size, it is not always possible to reliably estimate their frequency or establish a causal relationship to drug exposure.

Immune System Disorders:Hypersensitivity reactions, anaphylaxis, including anaphylactic shock, pruritus, rashes, eczema, urticaria, and dermatitis [see Contraindications (4), Warnings and Precautions (5.3)].

Skin and Subcutaneous Tissue Disorders: Eczematous eruptions (atopic dermatitis-like eruptions) [see Warnings and Precautions (5.6)].

7 DRUG INTERACTIONS

CYP450 Substrates

The formation of CYP450 enzymes can be altered by increased levels of certain cytokines (e.g., IL-1, IL-6, IL-10, TNFα, IFN) during chronic inflammation. Treatment with SILIQ may modulate serum levels of some cytokines.

Therefore, upon initiation or discontinuation of SILIQ in patients who are receiving concomitant drugs which are CYP450 substrates, particularly those with a narrow therapeutic index, consider monitoring for effect (e.g., for warfarin) or drug concentration (e.g., for cyclosporine) and consider dosage modification of the CYP450 substrate [see Clinical Pharmacology (12.3)].

8 USE IN SPECIFIC POPULATIONS

8.1 Pregnancy

Risk Summary

There are no human data on SILIQ use in pregnant women to inform a drug-associated risk. Human IgG antibodies are known to cross the placental barrier; therefore, SILIQ may be transmitted from the mother to the developing fetus. In a combined embryofetal development and pre- and postnatal development study, no adverse developmental effects were observed in infants born to pregnant monkeys after subcutaneous administration of brodalumab during organogenesis through parturition at doses up to 26 times the maximum recommended human dose (MRHD) [see Data].

The estimated background risk of major birth defects and miscarriage for the indicated population is unknown. In the U.S. general population, the estimated background risk of major birth defects and miscarriage in clinically recognized pregnancies is 2 to 4% and 15 to 20%, respectively.

Data

Animal Data

A combined embryofetal development and pre- and postnatal development study was conducted in cynomolgus monkeys administered brodalumab. No brodalumab-related effects on embryofetal toxicity or malformations, or on morphological, functional, or immunological development were observed in infants from pregnant monkeys administered weekly subcutaneous doses of brodalumab up to 26 times the MRHD from the beginning of organogenesis to parturition (on a mg/kg basis of 90 mg/kg/week).

8.2 Lactation

Risk Summary

There are no data on the presence of brodalumab in human milk, the effects on the breastfed infant, or the effects on milk production. Brodalumab was detected in the milk of lactating cynomolgus monkeys. The developmental and health benefits of breastfeeding should be considered along with the mother’s clinical need for SILIQ and any potential adverse effects on the breastfed infant from SILIQ or from the underlying maternal condition.

8.4 Pediatric Use

The safety and effectiveness of SILIQ have not been evaluated in pediatric patients.

8.5 Geriatric Use

Of the 3,066 plaque psoriasis subjects initially randomized to SILIQ in clinical trials, 192 (6%) were ≥ 65 years old and no subjects were ≥ 75 years old. Although no differences in safety or efficacy were observed between older and younger subjects, the number of subjects aged 65 years and older was not sufficient to determine whether they responded differently from younger subjects [see Clinical Pharmacology (12.3)].

11 DESCRIPTION

Brodalumab is a human monoclonal IgG2κ antibody directed against human interleukin-17 receptor A (IL-17RA). It is expressed in a Chinese Hamster Ovary (CHO) cell line. Brodalumab is comprised of 1312 amino acids and has an estimated molecular mass of 144,000 Daltons.

SILIQ (brodalumab) injection is a sterile, preservative-free, clear to slightly opalescent, colorless to slightly yellow solution delivered via subcutaneous injection. SILIQ is supplied in a single-dose syringe made from type 1 glass with stainless steel 27G x ½” needle. Each SILIQ single-dose prefilled syringe delivers 1.5 mL of solution containing 210 mg of brodalumab formulated in glutamate (6.5 mg), polysorbate 20 (0.15 mg), proline (36 mg), and Water for Injection, USP at pH 4.8.

12 CLINICAL PHARMACOLOGY

12.1 Mechanism of Action

Brodalumab is a human monoclonal IgG2 antibody that selectively binds to human IL-17RA and inhibits its interactions with cytokines IL-17A, IL-17F, IL-17C, IL-17A/F heterodimer, and IL-25. IL-17RA is a protein expressed on the cell surface and is a required component of receptor complexes utilized by multiple IL-17 family cytokines. Blocking IL-17RA inhibits IL-17 cytokine-induced responses including the release of pro-inflammatory cytokines and chemokines.

12.2 Pharmacodynamics

Elevated levels of IL-17A, IL-17C, and IL-17F are found in psoriatic plaques. Serum IL-17A levels, measured at Weeks 12, 24, and 48 of SILIQ 210 mg every 2 weeks of treatment, were higher than the baseline levels in subjects with moderate to severe plaque psoriasis. The relationship between the pharmacodynamic activity and the mechanism(s) by which brodalumab exerts its clinical effects is unknown.

12.3 Pharmacokinetics

Absorption

Following a single subcutaneous dose of 210 mg in subjects with plaque psoriasis, brodalumab reached peak mean (±SD) serum concentration (Cmax) of 13.4±7.3 mcg/mL by approximately 3 days post-dose. The mean (±SD) area-under-the-concentration-time curve (AUC) of brodalumab was 111±64 mcg•day/mL.

Following multiple subcutaneous doses of 210 mg every 2 weeks, steady-state was achieved by Week 4. The mean (±SD) Cmaxwas 20.6±14.6 mcg/mL and the mean (±SD) AUC over the 2-week dosing interval was 227±167 mcg•day/mL.

Following subcutaneous administration, brodalumab bioavailability was approximately 55%.

Distribution

Following a single subcutaneous administration of brodalumab 210 mg in subjects with plaque psoriasis, the mean (±SD) apparent volume of distribution (Vz/F) of brodalumab was 8.9±9.4 L.

Elimination

The metabolic pathway of brodalumab has not been characterized. As a human monoclonal IgG2 antibody, brodalumab is expected to be degraded into small peptides and amino acids via catabolic pathways in a manner similar to endogenous IgG.

Following a single subcutaneous administration of brodalumab 210 mg in subjects with plaque psoriasis, the mean (±SD) apparent total clearance (CL/F) was 3.0±3.5 L/day. The clearance of brodalumab increased with decreasing doses due to nonlinear elimination.

Dose Linearity

Brodalumab exhibited nonlinear pharmacokinetics with exposures that increased greater than dose-proportionally over a dose range from 140 mg (approximately 0.67 times the recommended dose) to 350 mg (approximately 1.67 times the recommended dose) following subcutaneous administrations in subjects with plaque psoriasis.

Weight

Brodalumab trough concentrations were lower in subjects with higher body weight.

Specific Populations

Hepatic or Renal Impairment

No trials were conducted to assess the effect of hepatic or renal impairment on the pharmacokinetics of brodalumab.

Age: Geriatric Population

Population pharmacokinetic analysis indicated that age did not significantly influence the clearance of brodalumab in subjects with plaque psoriasis. Subjects who were 65 years or older had a similar brodalumab clearance as compared to subjects less than 65 years old.

Drug Interaction Studies

In subjects with plaque psoriasis, one week following a single subcutaneous administration of 210 mg brodalumab, the exposure of midazolam (CYP3A4 substrate) was increased by 24% [see Drug Interactions (7)].

13 NONCLINICAL TOXICOLOGY

13.1 Carcinogenesis, Mutagenesis, Impairment of Fertility

Animal studies have not been conducted to evaluate the carcinogenic or mutagenic potential of SILIQ. The published literature is mixed on the potential effects on malignancy risk due to the inhibition of the IL-17RA, the pharmacological action of SILIQ. Some published literature suggests that IL-17A directly promotes cancer cell invasion, which suggests a potential beneficial effect of SILIQ. However, other reports indicate IL-17A promotes T-cell mediated tumor rejection, which suggests a potential adverse effect by SILIQ. However, inhibition of the IL-17RA with SILIQ has not been studied in these models. Therefore, the relevance of experimental findings in these models for malignancy risk in humans is unknown.

In cynomolgus monkeys, there were no effects on fertility parameters such as changes in reproductive organs or sperm analysis following subcutaneous administration of brodalumab at dose levels up to 90 mg/kg/week for 6 months (26 times the MRHD on a mg/kg basis). The monkeys were not mated in this study to evaluate effects on fertility.

14 CLINICAL STUDIES

Three multicenter, randomized, double-blind, controlled trials (Trials 1, 2, and 3) enrolled a total of 4373 subjects 18 years of age and older with at least a 6-month history of moderate to severe plaque psoriasis, defined as having a minimum affected body surface area (BSA) of 10%, a Psoriasis Area and Severity Index (PASI) score ≥ 12, a static Physician’s Global Assessment (sPGA) score ≥3 in the overall assessment (plaque thickness/induration, erythema, and scaling) of psoriasis on a severity scale of 0 to 5, and who were candidates for systemic therapy or phototherapy. In all three trials, subjects were randomized to subcutaneous treatment with placebo or SILIQ 210 mg at Weeks 0, 1, and 2, followed by treatments every 2 weeks [Q2W] through Week 12. In the two active comparator trials (Trials 2 and 3), subjects randomized to ustekinumab received a 45 mg dose if their weight was less than or equal to 100 kg and a 90 mg dose if their weight was greater than 100 kg at Weeks 0, 4, and 16, followed by the same dose every 12 weeks.

All three trials assessed the change from baseline to Week 12 compared to placebo in the two co-primary endpoints: 1) PASI 75, the proportion of subjects who achieved at least a 75% reduction in the PASI composite score that takes into consideration both the percentage of body surface area affected and the nature and severity of psoriatic changes (induration, erythema, and scaling) within the affected region, and 2) the proportion of subjects with an sPGA of 0 (clear) or 1 (almost clear), and at least a 2-point improvement from baseline. In Trials 2 and 3, comparisons were also made to ustekinumab for the primary endpoint of the proportion of subjects who achieved a reduction in PASI score of 100% (PASI 100) from baseline at Week 12.

Other evaluated outcomes included the proportion of subjects who achieved an sPGA of 0 (clear) at Week 12, and the proportion of subjects who achieved a Psoriasis Symptom Inventory (PSI) score of 0 (not at all) or 1 (mild) on every item (itch, redness, scaling, burning, stinging, cracking, flaking, and pain) at Week 12. Baseline demographics and disease characteristics were generally consistent across all treatment groups in all three trials. Subjects were predominantly men (69%) and white (91%), with a mean age of 45 years. The mean baseline body weight was 90.5 kg and 28% of subjects had body weight greater than 100 kg. The baseline PASI score ranged from 9.4 to 72 (median: 17.4) and the baseline- affected BSA ranged from 10 to 97% (median: 21%). Baseline sPGA scores ranged from “3 (moderate)” (58%) to “5 (very severe)” (5%).

Approximately 21% of subjects had a history of psoriatic arthritis. Approximately 30% of subjects had previously received a biologic therapy and 12% of subjects had failed previous biologic therapy.

Clinical Response at Week 12

The results of Trials 1, 2, and 3 are presented in Table 2.

Table 2: Efficacy Results at Week 12n Adults with Plaque Psoriasis in Trials 1, 2, and 3 (NRI [NRI = non-responder imputation])
Endpoint | Trial 1 |  | Trial 2 |  |  | Trial 3
Endpoint | SILIQ; 210 mg Q2W; (N=222); n (%) | Placebo; (N=220); n (%) | SILIQ; 210 mg Q2W; (N=612); n (%) | Ustekinumab; (N=300); n (%) | Placebo; (N=309); n (%) | SILIQ; 210 mg Q2W; (N=624); n (%) | Ustekinumab; (N=313); n (%) | Placebo; (N=315); n (%)
PASI 75 [Co-primary endpoints] response | 185 (83) | 6 (3) | 528 (86) | 210 (70) | 25 (8) | 531 (85) | 217 (69) | 19 (6)
PASI 100; response | 93 (42) | 1 (<1) | 272 (44) | 65 (22) | 2 (1) | 229 (37) | 58 (19) | 1 (<1)
sPGA success clear (0) or almost clear (1) | 168 (76) | 3 (1) | 481 (79) | 183 (61) | 12 (4) | 497 (80) | 179 (57) | 13 (4)
sPGA of; clear (0) | 93 (42) | 1 (<1) | 274 (45) | 65 (21) | 2 (1) | 229 (37) | 58 (19) | 1 (<1)

Examination of age, gender, race, use of prior systemic or phototherapy, and use of prior biologics did not identify differences in response to SILIQ among these subgroups.

At Week 12, compared to subjects in the placebo group, a greater proportion of subjects in SILIQ 210 mg Q2W group achieved a Psoriasis Symptom Inventory (PSI) score of 0 (not at all) or 1 (mild) on every item (itch, redness, scaling, burning, stinging, cracking, flaking, pain).

Maintenance of Effect

In Trial 1, subjects randomized to receive SILIQ and who were responders at Week 12 (i.e., sPGA of 0 or 1) were re-randomized to receive either placebo or SILIQ. Among responders at Week 12, 83% (69/83) of subjects re-randomized to continued treatment with SILIQ 210 mg Q2W maintained this response (sPGA of 0 or 1) at Week 52 compared to none (0/84) who were re-randomized to placebo and withdrawn from SILIQ. In addition, 87% (72/83) of subjects re-randomized to continued treatment with SILIQ 210 mg Q2W achieved PASI 75 response at Week 52 compared to none (0/84) who were re-randomized to placebo and withdrawn from SILIQ.

Trials 2 and 3 included a re-randomized phase during which subjects originally randomized to receive SILIQ during the first 12 weeks were re-randomized to one of four SILIQ regimens at the Week 12 visit and placebo subjects were crossed over to receive SILIQ 210 mg Q2W. Subjects receiving ustekinumab continued the same treatment until crossed over at Week 52 to SILIQ 210 mg Q2W. For sPGA 0 or 1 responders at Week 12, the percentage of subjects who maintained this response at Week 52 was 79% for subjects treated with SILIQ 210 mg Q2W. For PASI 100 responders at Week 12, 72% of the subjects who continued on SILIQ 210 mg Q2W maintained the response at Week 52.

16 HOW SUPPLIED/STORAGE AND HANDLING

How Supplied

SILIQ®(brodalumab) injection is available in a single-dose prefilled syringe containing a sterile, preservative-free clear to slightly opalescent, colorless to slightly yellow solution.

- NDC 0187-0004-02: Carton of two 210 mg/1.5 mL single-dose prefilled syringes

Storage and Handling

- Store refrigerated at 2°C to 8°C (36°F to 46°F) in the original carton to protect from light and physical damage during storage.
- When necessary, prefilled syringes can be stored at room temperature up to a maximum of 77°F (25°C) in the original carton for a maximum single period of 14 days with protection from light and sources of heat. Once the prefilled syringe has reached room temperature, do not place back into the refrigerator. Discard after 14 days at room temperature.
- Do not freeze.
- Do not shake.

17 PATIENT COUNSELING INFORMATION

Advise the patient to read the FDA-approved patient labeling (Medication Guideand Instructions for Use) before the patient starts using SILIQ, and each time the prescription is renewed, as there may be new information they need to know.

Suicidal Thoughts and Behavior

Instruct patients and their caregivers to monitor for the emergence of suicidal thoughts and behavior and promptly seek medical attention if the patient experiences suicidal thoughts, new or worsening depression, anxiety, or other mood changes [see Warnings and Precautions (5.1)].

Instruct patients to carry the wallet card provided and to call the National Suicide Prevention Lifeline at 1-800-273-8255 if they experience suicidal thoughts.

SILIQ REMS Program

Because of the observed suicidal thoughts and behavior in subjects treated with SILIQ, SILIQ is available only through a restricted program called the SILIQ REMS Program [see Warnings and Precautions (5.2)].Inform the patient of the following:

- Patients must enroll in the program [see Warnings and Precautions (5.1,5.2)].
- Patients will be given a SILIQ Patient Wallet Card that they should carry with them at all times. This card describes symptoms which, if experienced, should prompt the patient to immediately seek medical evaluation. Advise the patient to show the SILIQ Patient Wallet Card to other treating healthcare providers.

SILIQ is available only from certified pharmacies participating in the program. Therefore, provide patients with the telephone number and website for information on how to obtain the product.

Hypersensitivity Reactions

Advise patients to seek immediate medical attention if they experience any symptoms of serious hypersensitivity reactions [see Warnings and Precautions (5.3)].

Infections

Inform patients that SILIQ may lower the ability of their immune system to fight infections. Instruct patients of the importance of communicating any history of infections to their healthcare providers and to contact their healthcare providers if they develop any signs or symptoms of infection [ see Warnings and Precautions (5.4)].

Eczematous Eruptions

Inform patients that skin reactions resembling eczema may occur with the use of SILIQ. Instruct patients to seek medical advice if they develop signs or symptoms of eczema [see Warnings and Precautions (5.6)].

Crohn’s Disease

Instruct patients to seek medical advice if they develop signs and symptoms of Crohn’s disease [ see Warnings and Precautions (5.7)].

Immunization

Instruct patients to inform their healthcare provider that they are taking SILIQ prior to a potential vaccination [see Warnings and Precautions (5.8)].

Instructions for Injection

Instruct the patient to perform the first self-injection under the guidance and supervision of a qualified healthcare professional for proper training in subcutaneous injection technique.

Instruct patients who are self-administering to inject the full dose of SILIQ [see Dosage and Administration (2.2) and Instructions for Use].

Instruct patients or caregivers in the technique of proper syringe and needle disposal [see Instructions for Use].

Distributed by:
Bausch Health US, LLC
Bridgewater, NJ 08807 USA

Manufactured by:
Bausch Health Ireland, Limited
Dublin, Leinster, Ireland 24

U.S. License Number: 2365

Patented. See https://patents.ortho-dermatologics.com for US patent information.

SILIQ is a trademark of Bausch Health Companies Inc. or its affiliates.

© 2024 Bausch Health Companies Inc. or its affiliates

9643802

Medication Guide

Siliq®(sil-eek)

(brodalumab)

Injection, for subcutaneous use

What is the most important information I should know about SILIQ?

SILIQ may cause serious side effects, including:

- Suicidal thoughts and behavior have happened insome people treated with SILIQ. Some people have ended their own lives. Your risk of suicidal thoughts and behavior may be increased if you have a history of suicidal thoughts or depression. It is not known if SILIQ causes suicidal thoughts and behavior. Get medical help right away or call the National Suicide and Crisis Lifeline at 988, if you or your caregiver notice in you any of the following symptoms:
- new or worsening depression or anxiety
- thoughts of suicide, dying, or hurting yourself
- changes in behavior or mood
- acting on dangerous impulses
- attempt to commit suicide

Because of your risk of suicidal thoughts and behavior during your treatment with SILIQ, SILIQ is available only through a restricted distribution program called the SILIQ Risk Evaluation and Mitigation Strategy (REMS). Before you can receive SILIQ:

- Your healthcare provider must:
  - enroll in the SILIQ REMS
  - give you a SILIQ Patient Wallet Cardwhich explains the symptoms you should get medical help for right away
- You must:
  - sign a Patient-Prescriber Agreement Form
  - carry the Patient Wallet Cardwith you at all times during treatment with SILIQ

SILIQ is only available through pharmacies that participate in the SILIQ REMS. Your healthcare provider can give you information about how to find a participating pharmacy. For more information, go to www.SILIQREMS.com or call 1-855-511-6135.

- Serious allergic reactions.Get medical help right away if you get any of the following signs or symptoms of a serious allergic reaction:
- swelling of the face, lips, or tongue
- trouble breathing or swallowing
- itching
- dizziness or feel faint
- rash, hives, or redness all over your body
- chest pain or tightness
- Serious infections.SILIQ may lower the ability of your immune system to fight infections and may increase your risk of infections. Your healthcare provider will check you for tuberculosis (TB) before starting treatment with SILIQ and may treat you for TB before you begin treatment with SILIQ if you have a history of TB or have active TB. Your healthcare provider should watch you closely for signs and symptoms of infection and TB during and after treatment with SILIQ.
- Tell your healthcare provider right away if you develop any symptoms of an infection, including:
- fever, sweats, or chills
- muscle aches
- cough
- shortness of breath
- sore throat or difficulty swallowing
- warm, red, or painful skin or sores on your body
- diarrhea or stomach pain
- burning when you urinate or urinate more often than normal

See “What are the possible side effects of SILIQ?”for more information about side effects.

What is SILIQ?

SILIQ is a prescription medicine used to treat adults with moderate to severe plaque psoriasis:

- who may benefit from taking injections or pills (systemic therapy) or phototherapy (ultraviolet light treatment), and
- who have not responded or lost response to other systemic therapy.

It is not known if SILIQ is safe and effective in children.

Do not use SILIQ if you:

- have Crohn’s disease.
- are allergic to brodalumab or any of the ingredients in SILIQ. See the end of this Medication Guide for a list of ingredients in SILIQ.

Before you use SILIQ, tell your healthcare provider about all of your medical conditions, including if you:

- have a history of mental problems, including suicidal thoughts, depression, anxiety, or mood problems.
- have an infection that does not go away or that keeps coming back.
- have TB or have been in close contact with someone with TB.
- have recently received or are scheduled to receive an immunization (vaccine). You should avoid receiving live vaccines during treatment with SILIQ.
- are pregnant or plan to become pregnant. It is not known if SILIQ can harm your unborn baby.
- are breastfeeding or plan to breastfeed. It is not known if SILIQ passes into your breast milk.

Tell your healthcare provider about all the medicines you take,including prescription and over-the-counter medicines, vitamins, and herbal supplements.

How should I use SILIQ?

- See the detailed “Instructions for Use” that comes with SILIQ for information on how to inject a dose of SILIQ and how to properly throw away (dispose of) used SILIQ prefilled syringes.
- Use SILIQ exactly as your healthcare provider tells you to use it.
- Your healthcare provider may stop SILIQ if your plaque psoriasis does not improve within 12 to 16 weeks of treatment.

What are the possible side effects of SILIQ?

SILIQ may cause serious side effects.

- See “What is the most important information I should know about SILIQ?”
- Severe skin reactions that look like eczemacan happen during treatment with SILIQ from days to months after your first dose and can sometimes lead to hospitalization. Your healthcare provider may temporarily stop treatment with SILIQ if you develop severe skin reactions. Tell your healthcare provider if you have any of the following signs or symptoms:
- redness or rash
  - itching
  - small bumps or patches
  - your skin is dry or feels like leather
  - blisters on the hands or feet that ooze or become crusty
  - skin peeling
- Crohn’s disease.Tell your healthcare provider if you develop diarrhea, painful diarrhea, bloody stools, stomach pain or cramping, sudden or uncontrollable bowel movements, loss of appetite, constipation, weight loss, fever, or tiredness.

The most common side effects of SILIQ include:joint pain, headache, tiredness, diarrhea, mouth or throat pain, nausea, muscle pain, injection site reactions, flu (influenza), low white blood count (neutropenia), and fungal infections of the skin.

These are not all the possible side effects of SILIQ.

Call your doctor for medical advice about side effects. You may report side effects to FDA at 1-800-FDA-1088.

How should I store SILIQ?

- Store SILIQ prefilled syringe in the refrigerator at 36°F to 46°F (2°C to 8°C).
- If needed, SILIQ prefilled syringe may be stored at room temperature up to 77°F (25°C) up to 14 days. Do notplace SILIQ prefilled syringe stored at room temperature back into the refrigerator.
- Throw away SILIQ prefilled syringe that has been stored at room temperature after 14 days.
- Protect SILIQ prefilled syringe from heat.
- Do notfreeze.
- Do notshake.
- Keep SILIQ prefilled syringe in the original carton to protect from light and physical damage.

Keep SILIQ and all medicines out of the reach of children.

General information about safe and effective use of SILIQ.

Medicines are sometimes prescribed for purposes other than those listed in a Medication Guide. Do not use SILIQ for a condition for which it was not prescribed. Do not give SILIQ to other people even if they have the same symptoms that you have. It may harm them. You can ask your pharmacist or healthcare provider for information about SILIQ that is written for health professionals.

What are the ingredients in SILIQ?

Active ingredient: brodalumab

Inactive ingredients: glutamate, polysorbate 20, proline, and Water for Injection.

Distributed by:Bausch Health US, LLC

Bridgewater, NJ 08807 USA

Manufactured by:Bausch Health Ireland, Limited

Dublin, Leinster, Ireland 24

U.S. License Number: 2365

Patented. See https://patents.ortho-dermatologics.com for US patent information.

SILIQ is a trademark of Bausch Health Companies Inc. or its affiliates.

© 2024 Bausch Health Companies Inc. or its affiliates

9643802

For more information, go to www.SILIQ.com or call Bausch Health US, LLC at 1-800-321-4576.

This Medication Guide has been approved by the U.S. Food and Drug Administration. Revised: 08/2024

Instructions for Use

SILIQ is supplied as a single-dose prefilled syringe. Each prefilled syringe contains one 210 mg dose of SILIQ. Each SILIQ prefilled syringe can only be used one time.

Your healthcare provider has prescribed SILIQ and will tell you how often it should be injected. If your healthcare provider decides that you or a caregiver may be able to give your injections of SILIQ at home, you should receive training on the right way to prepare and inject SILIQ. Do not try to inject yourself until you have been shown the right way to give the injections by your healthcare provider.

Read all of the instructions before using the SILIQ prefilled syringe. Call your healthcare provider if you or your caregiver have any questions about the right way to inject SILIQ.

INSTRUCTIONS FOR USE

Siliq®(sil-eek)

(brodalumab)

Injection, for subcutaneous use

Single-Dose Prefilled Syringe

Guide to parts

Important:Needle is inside the gray needle cap.

Important

Storing your SILIQ prefilled syringe

- Store SILIQ prefilled syringe in the refrigerator at 36°F to 46°F (2°C to 8°C) in the original carton to protect from light and physical damage.
- If needed, SILIQ prefilled syringe may be stored at room temperature up to 77°F (25°C) for up to 14 days. Do notplace SILIQ prefilled syringe stored at room temperature back into the refrigerator.
- Throw away SILIQ prefilled syringe that has been stored at room temperature after 14 days.
- Protect SILIQ prefilled syringe from heat.
- Do notfreeze.
- Do notshake.
- Keep SILIQ prefilled syringe in the original carton to protect from light and physical damage.
- Keep SILIQ prefilled syringe and all medicines out of the reach of children.

Using your SILIQ prefilled syringe

- It is important that you do not try to give the injection unless you or your caregiver has received training from your healthcare provider.
- Do notuse a SILIQ prefilled syringe after the expiration date on the label.
- Do notshake the SILIQ prefilled syringe.
- Do notremove the gray needle cap from the SILIQ prefilled syringe until you are ready to inject.
- Do notuse a SILIQ prefilled syringe if it has been dropped on a hard surface. Part of the SILIQ prefilled syringe may be broken even if you cannot see the break. Use a new SILIQ prefilled syringe, and call 1-800-321-4576.

Step 1: Prepare

A Remove one SILIQ prefilled syringe from the package.

Grab the syringe by the barrel to remove the prefilled syringe from the tray.

Place your finger or thumb Grab Here

on the edge of the tray to

hold it while you remove

the prefilled syringe.

Put the original package with any unused prefilled syringes back in the refrigerator.

For safety reasons:

- Do notgrab the plunger rod.
- Do notgrab the gray needle cap.
- Do notremove the gray needle cap until you are ready to inject.

Wait about 30 minutes to let the prefilled syringe warm to room temperature before you use it.

- Do notput the prefilled syringe back in the refrigerator after it has reached room temperature.
- Do nottry to warm the prefilled syringe by using a heat source such as hot water or microwave.
- Do notleave the prefilled syringe in direct sunlight.
- Do notshake the prefilled syringe.

Important: Always hold the prefilled syringe by the syringe barrel.

B Inspect the SILIQ prefilled syringe.

Make sure the medicine in the prefilled syringe is clear and colorless to slightly yellow.

- Do notuse the syringe if:
- The medicine is cloudy or discolored or contains flakes or particles.
- Any part appears cracked or broken.
- The gray needle cap is missing or not securely attached.
- The expiration date printed on the label has passed.

In all cases, use a new prefilled syringe, and call 1-800-321-4576.

C Gather all materials needed for your injection.

Wash your hands thoroughly with soap and water.

On a clean, well-lit work surface, place the:

- Prefilled syringe
- Alcohol wipes
- Cotton ball or gauze pad
- Adhesive bandage
- Sharps disposal container

D Prepare and clean your injection site.

You can use:

- Your thigh
- Stomach area (abdomen), except for a 2-inch area right around your navel (belly button)
- Outer area of upper arm (only if someone else is giving you the injection)

Clean your injection site with an alcohol wipe. Let your skin dry.

- Do nottouch this area again before injecting.
- Choose a different site each time you give yourself an injection. If you want to use the same injection site, make sure it is not the same spot on the injection site that you used for a previous injection.
- Do notinject into areas where the skin is tender, bruised, red, or hard. Avoid injecting into areas with scars or stretch marks.
- Avoid injecting directly into raised, thick, red, or scaly skin patch or lesion.

Step 2: Get ready

EPull the gray needle cap straight off and away from your body when you are ready to inject.

It is normal to see a drop of liquid at the end of the needle.

- Do nottwist or bend the gray needle cap.
- Do notput the gray needle cap back onto the prefilled syringe.
- Do notremove the gray needle cap from the prefilled syringe until you are ready to inject.

Important:Throw the needle cap into the sharps disposal container provided.

F Pinch your injection site to create a firm surface.

Pinch skin firmly between your thumb and fingers, creating an area about 2inches wide.

Important:Keep skin pinched while injecting.

Step 3: Inject

GHold the pinch. Insert the needle into your skin at 45 to 90 degrees.

Do notplace your finger on the plunger rod while inserting the needle.

HUsing slow and constant pressure, push the plunger rod all the way down until it reaches the bottom.

IWhen done, release your thumb, and gently lift the syringe and pull the needle out of your skin.

JInspect the syringe. If there is still medicine in the syringe barrel, this means you have not received a full dose. Call your healthcare provider right away.

Step 4: Finish

KDiscard (throw away) the used syringe.

- Put the used SILIQ syringe in an FDA-cleared sharps disposal container right away after use. Do notthrow away (dispose of) the syringe in your household trash.
- If you do not have an FDA-cleared sharps disposal container, you may use a household container that is:
- made of a heavy-duty plastic,
- can be closed with a tight-fitting, puncture-resistant lid, without sharps being able to come out,
- upright and stable during use,
- leak-resistant, and
- properly labeled to warn of hazardous waste inside the container.
- When your sharps disposal container is almost full, you will need to follow your community guidelines for the right way to dispose of your sharps disposal container. There may be state or local laws about how you should throw away used needles and syringes. For more information about safe sharps disposal, and for specific information about sharps disposal in the state that you live in, go to the FDA’s website at: http://www.fda.gov/safesharpsdisposal.
- Do notreuse the syringe.
- Do notrecycle the syringe or sharps disposal container or throw them into household trash.

Important:Always keep the sharps disposal container out of the reach of children.

L Examine the injection site.

If there is blood, press a cotton ball or gauze pad on your injection site. Do notrub the injection site. Apply an adhesive bandage if needed.

Distributed by:
Bausch Health US, LLC
Bridgewater, NJ 08807 USA

Manufactured by:
Bausch Health Ireland, Limited
Dublin, Leinster, Ireland 24

U.S. License Number: 2365

Patented. See https://patents.ortho-dermatologics.com for US patent information.

SILIQ is a trademark of Bausch Health Companies Inc. or its affiliates.

© 2024 Bausch Health Companies Inc. or its affiliates

For more information, go to www.SILIQ.com or call Bausch Health US, LLC at 1-800-321-4576.

This Instructions for Use has been approved by the U.S. Food and Drug Administration.

9643802 Revised: 08/2024

PACKAGE/LABEL PRINCIPAL DISPLAY PANEL

Contains 2 Single-Dose Prefilled Syringes

NDC0187-0004-02

SILIQ®
(brodalumab)
Injection
210 mg/1.5 mL

For Subcutaneous Use Only

See package insert for dosing
information and Instructions for Use.
Carton contents:
• 2 Prefilled Syringes
• 1 Package Insert
• 1 Instructions for Use
• 1 Medication Guide

ATTENTION: Dispense with enclosed Medication Guide.
Sterile Solution – No Preservative
KEEP OUT OF REACH OF CHILDREN.

Rx only